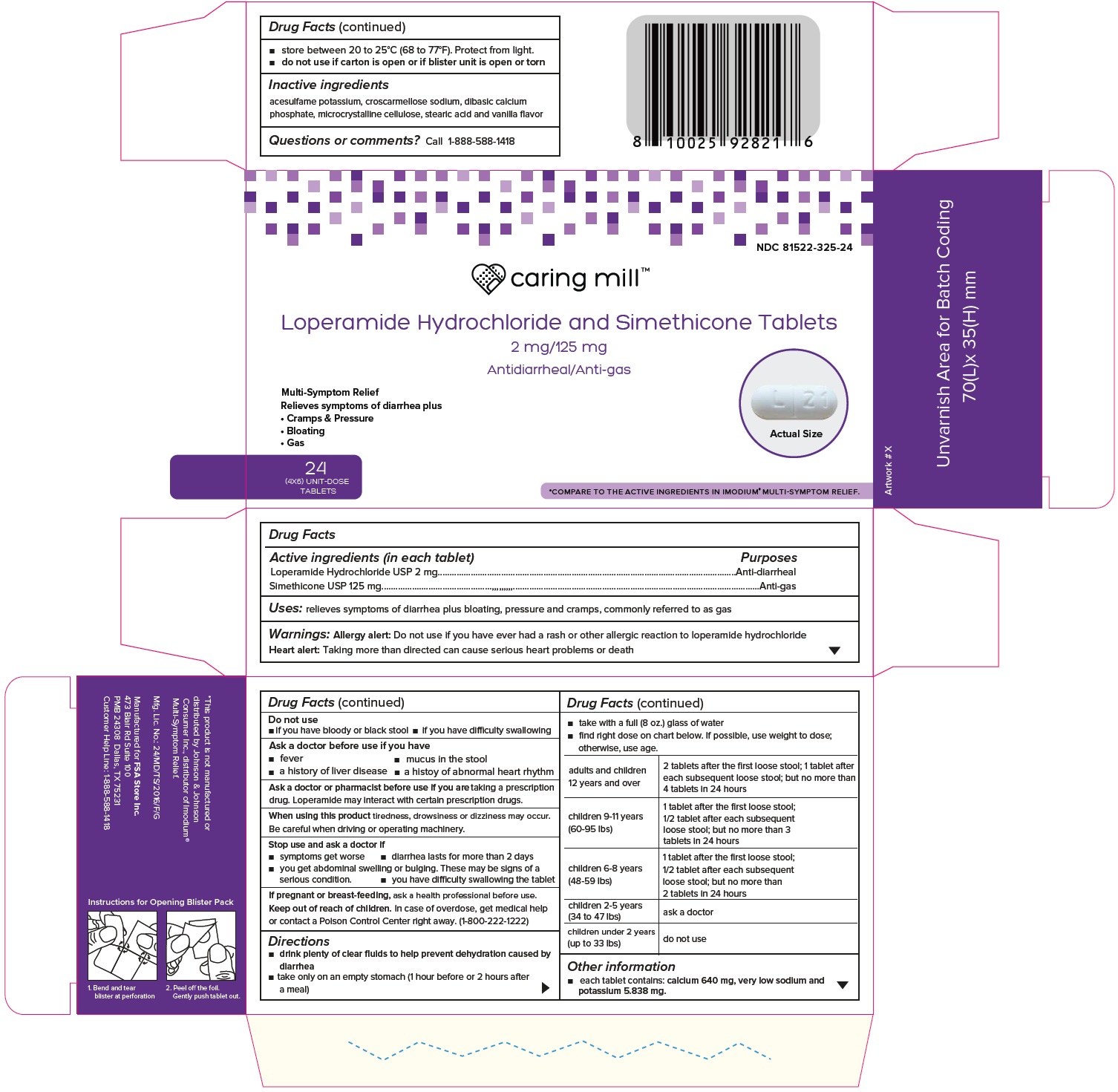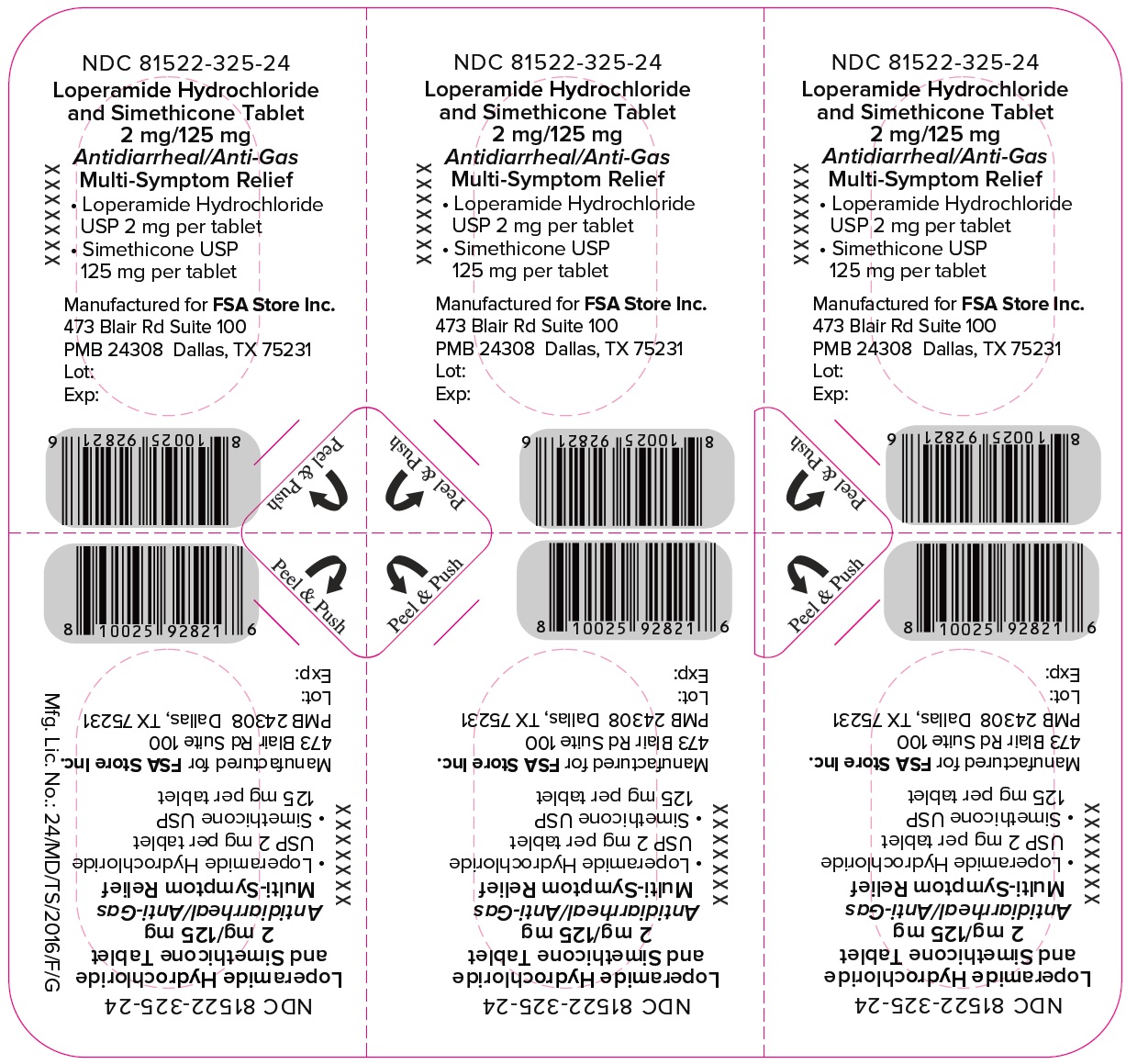 DRUG LABEL: Loperamide Hydrochloride and Simethicone

NDC: 81522-325 | Form: TABLET
Manufacturer: FSA store INC
Category: otc | Type: HUMAN OTC DRUG LABEL
Date: 20250405

ACTIVE INGREDIENTS: LOPERAMIDE HYDROCHLORIDE 2 mg/1 1; DIMETHICONE 125 mg/1 1
INACTIVE INGREDIENTS: ACESULFAME POTASSIUM; CROSCARMELLOSE SODIUM; ANHYDROUS DIBASIC CALCIUM PHOSPHATE; MICROCRYSTALLINE CELLULOSE; STEARIC ACID

Loperamide Hydrochloride and Simethicone Tablets, 2 mg/125 mg (OTC)

ACTIVE INGREDIENT(S)

(in each tablet)
Loperamide Hydrochloride USP 2 mg
Simethicone USP 125 mg

PURPOSES

Anti-diarrheal
Anti-gas

USE(S)

relieves symptoms of diarrhea plus bloating, pressure and cramps, commonly referred to as gas

WARNINGS

Allergy alert:Do not use if you have ever had a rash or other allergic reaction to loperamide hydrochloride
Heart alert:Taking more than directed can cause serious heart problems or death

DO NOT USE

• if you have bloody or black stool
• if you have difficulty swallowing

ASK A DOCTOR BEFORE USE IF YOU HAVE

• fever
• mucus in the stool
• a history of liver disease

• a history of abnormal heart rhythm

ASK A DOCTOR OR PHARMACIST BEFORE USE IF

you aretaking a prescription drug. Loperamide may interact with certain prescription drugs.

WHEN USING THIS PRODUCT

tiredness, drowsiness or dizziness may occur. Be careful when driving or operating machinery.

STOP USE AND ASK A DOCTOR IF

• symptoms get worse
• diarrhea lasts for more than 2 days
• you get abdominal swelling or bulging. These may be signs of a serious condition.
• you have difficulty swallowing the tablet

PREGNANCY OR BREAST FEEDING

If pregnant or breast-feeding,ask a health professional before use.

KEEP OUT OF REACH OF CHILDREN

In case of overdose, get medical help or contact a Poison Control Center right away. (1-800-222-1222)

DIRECTIONS

• drink plenty of clear fluids to help prevent dehydration caused by diarrhea
• take only on an empty stomach (1 hour before or 2 hours after a meal)
• take with a full (8 oz.) glass of water
• find right dose on chart below. If possible, use weight to dose; otherwise, use age.

adults and children 12 years and over | 2 tablets after the first loose stool; 1 tablet after each subsequent loose stool; but no more than 4 tablets in 24 hours
children 9-11 years (60-95 lbs) | 1 tablet after the first loose stool; 1/2 tablet after each subsequent loose stool; but no more than 3 tablets in 24 hours
children 6-8 years (48-59 lbs) | 1 tablet after the first loose stool; 1/2 tablet after each subsequent loose stool; but no more than 2 tablets in 24 hours
children 2-5 years (34 to 47 lbs) | ask a doctor
children under 2 years (up to 33 lbs) | do not use

OTHER INFORMATION

• each tablet contains: calcium 640 mg, very low sodium and potassium 5.838 mg
• store between 20 to 25°C (68 to 77°F). Protect from light.
• do not use if carton is open or if blister unit is open or torn

INACTIVE INGREDIENTS

acesulfame potassium, croscarmellose sodium, dibasic calcium phosphate, microcrystalline cellulose, stearic acid and vanilla flavor

QUESTIONS OR COMMENTS

call 1-888-588-1418

Manufactured for FSA Store Inc.
473 Blair Rd Suite 100
PMB 24308 Dallas, TX 75231
Customer Help Line: 1-888-588-1418

PRINCIPAL DISPLAY PANEL

Loperamide Hydrochloride and Simethicone Tablets 2 mg/125 mg-1x6's carton

Loperamide Hydrochloride and Simethicone Tablets 2 mg/125 mg-6's foil